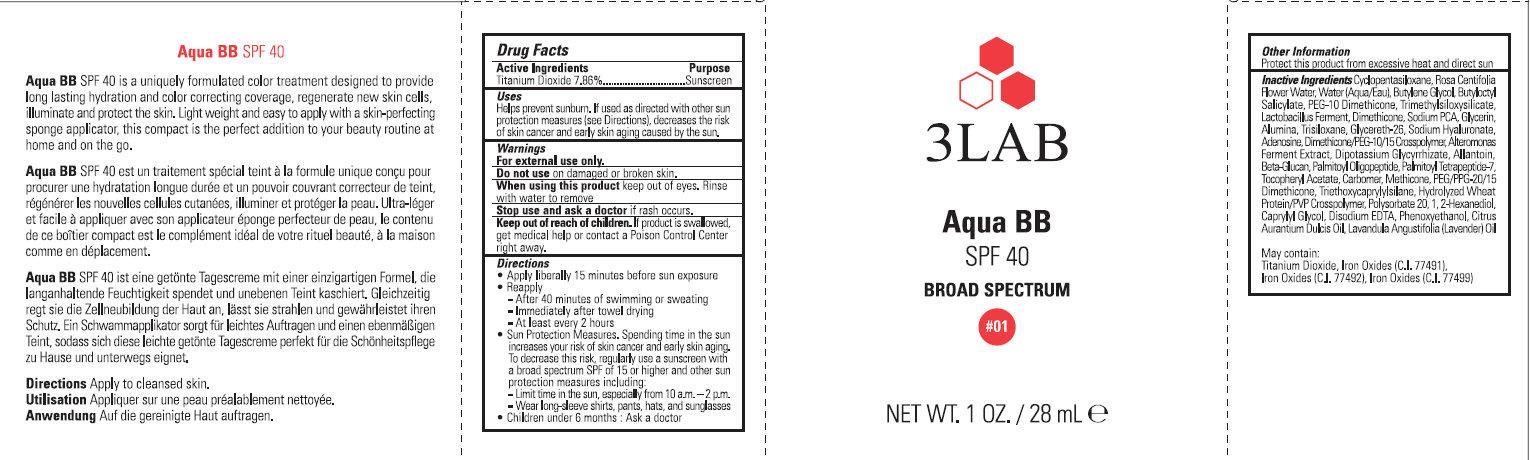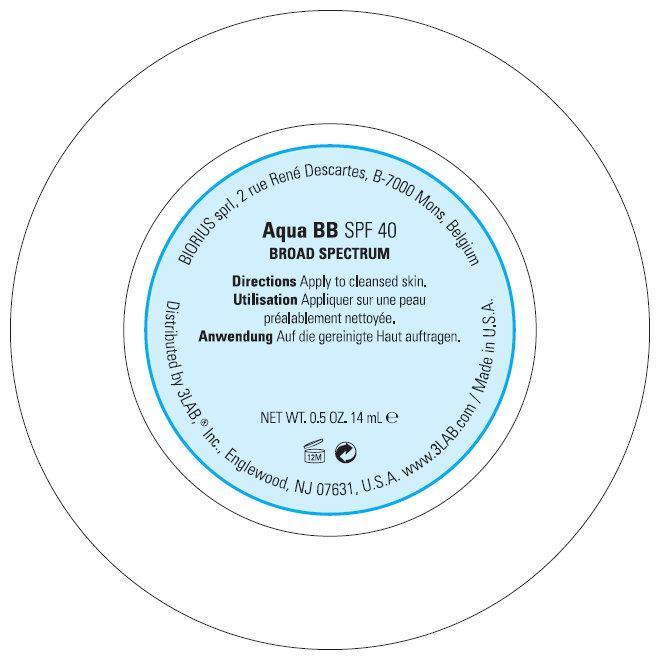 DRUG LABEL: 3LAB Aqua BB SPF 40 BROAD SPECTRUM 01
NDC: 76159-004 | Form: CREAM
Manufacturer: 3LAB, Inc.
Category: otc | Type: HUMAN OTC DRUG LABEL
Date: 20231212

ACTIVE INGREDIENTS: TITANIUM DIOXIDE 78.6 mg/1 mL
INACTIVE INGREDIENTS: TRIETHOXYCAPRYLYLSILANE; POLYSORBATE 20; 1,2-HEXANEDIOL; CYCLOMETHICONE 5; ROSA CENTIFOLIA FLOWER OIL; WATER; BUTYLENE GLYCOL; BUTYLOCTYL SALICYLATE; DIMETHICONE; SODIUM PYRROLIDONE CARBOXYLATE; GLYCERIN; ALUMINUM OXIDE; TRISILOXANE; GLYCERETH-26; HYALURONATE SODIUM; ADENOSINE; GLYCYRRHIZINATE DIPOTASSIUM; ALLANTOIN; PALMITOYL OLIGOPEPTIDE; PALMITOYL TETRAPEPTIDE-7; .ALPHA.-TOCOPHEROL ACETATE; PEG/PPG-20/15 DIMETHICONE; CAPRYLYL GLYCOL; EDETATE DISODIUM; PHENOXYETHANOL; LAVENDER OIL; FERRIC OXIDE RED; FERRIC OXIDE YELLOW; FERROSOFERRIC OXIDE

3LAB Aqua BB SPF 40 BROAD SPECTRUM #01

Active Ingredient

Titanium Dioxide 7.86%

Purpose

Sunscreen

Uses

Helps prevent sunburn. If used as directed with other sun protection measures (see Directions), decreases the risk of skin cancer and early skin aging caused by the sun.

Warnings

For external use only.

Do not use

on damaged or broken skin.

When using this product

keep out of eyes. Rinse with water to remove

Stop use and ask a doctor

if rash occurs.

Keep out of reach of children.

If product is swallowed, get medical help or contact a Poison Control Center right away.

Directions

- Apply liberally 15 minutes before sun exposure
- Reapply - After 40 minutes of swimming or sweating - Immediately after towel drying - At least every 2 hours
- Sun Protection Measures. Spending time in the sun increases your risk of skin cancer and early skin aging. To decrease this risk, regularly use a sunscreen with a broad spectrum SPF of 15 or higher and other sun protection measures including: - Limit time in the sun, especially from 10 a.m. - 2 p.m. - Wear long-sleeve shirts, pants, hats, and sunglasses
- Children under 6 months : Ask a doctor

Other Information

Protect this product from excessive heat and direct sun

Inactive Ingredients

Cyclopentasiloxane, Rosa Centifolia Flower Water, Water (Aqua/Eau), Butylene Glycol, Butyloctyl Salicylate, PEG-10 Dimethicone, Trimethylsiloxysilicate, Lactobacillus Fermentum, Dimethicone, Sodium PCA, Glycerin, Alumina, Trisiloxane, Glycereth-26, Sodium Hyaluronate, Adenosine, Dimethicone/PEG-10/15 Crosspolymer, Alteromonas Ferment Extract, Dipotassium Glycyrrhizate, Allantoin, Beta-Glucan, Palmitoyl Oligopeptide, Palmitoyl Tetrapeptide-7, Tocopheryl Acetate, Carbomer, Methicone, PEG/PPG-20/15 Dimethicone, Triethoxycaprylylsilane, Hydrolyzed Wheat Protein/PVP Crosspolymer, Polysorbate 20, 1,2-Hexanediol, Caprylyl Glycol, Disodium EDTA, Phenoxyethanol, Citrus Aurantium Dulcis Oil, Lavandula Angustifolia (Lavender) Oil May contain: Titanium Dioxide, Iron Oxides (C.I. 77491), Iron Oxides (C.I. 77492), Iron Oxides (C.I. 77499)